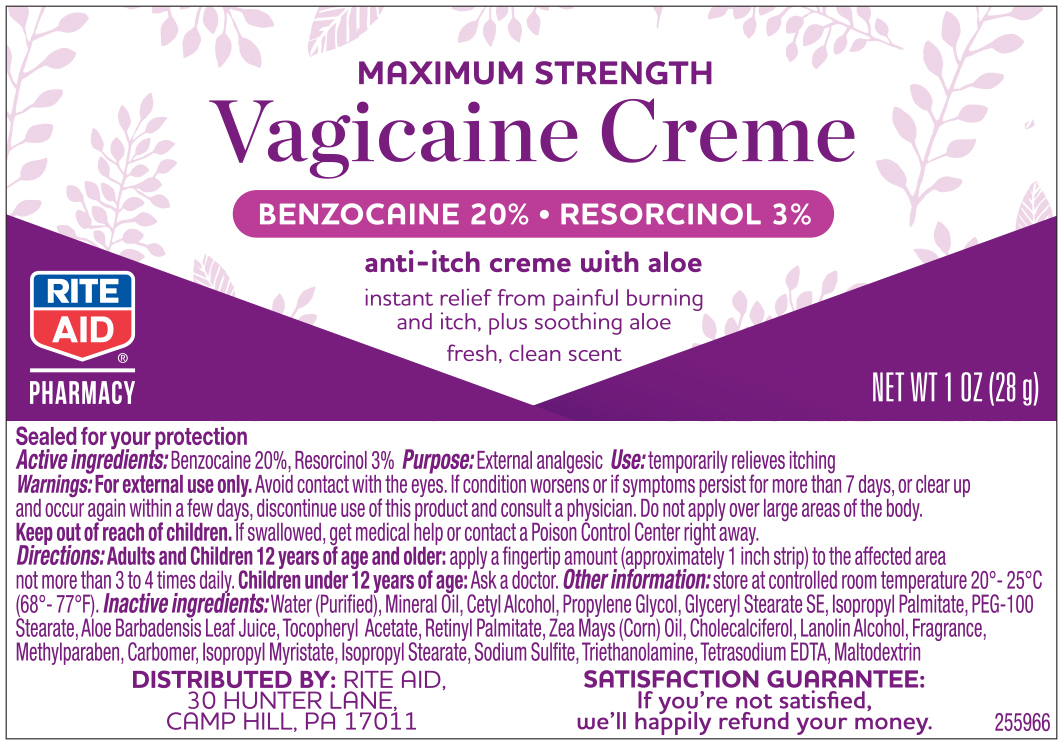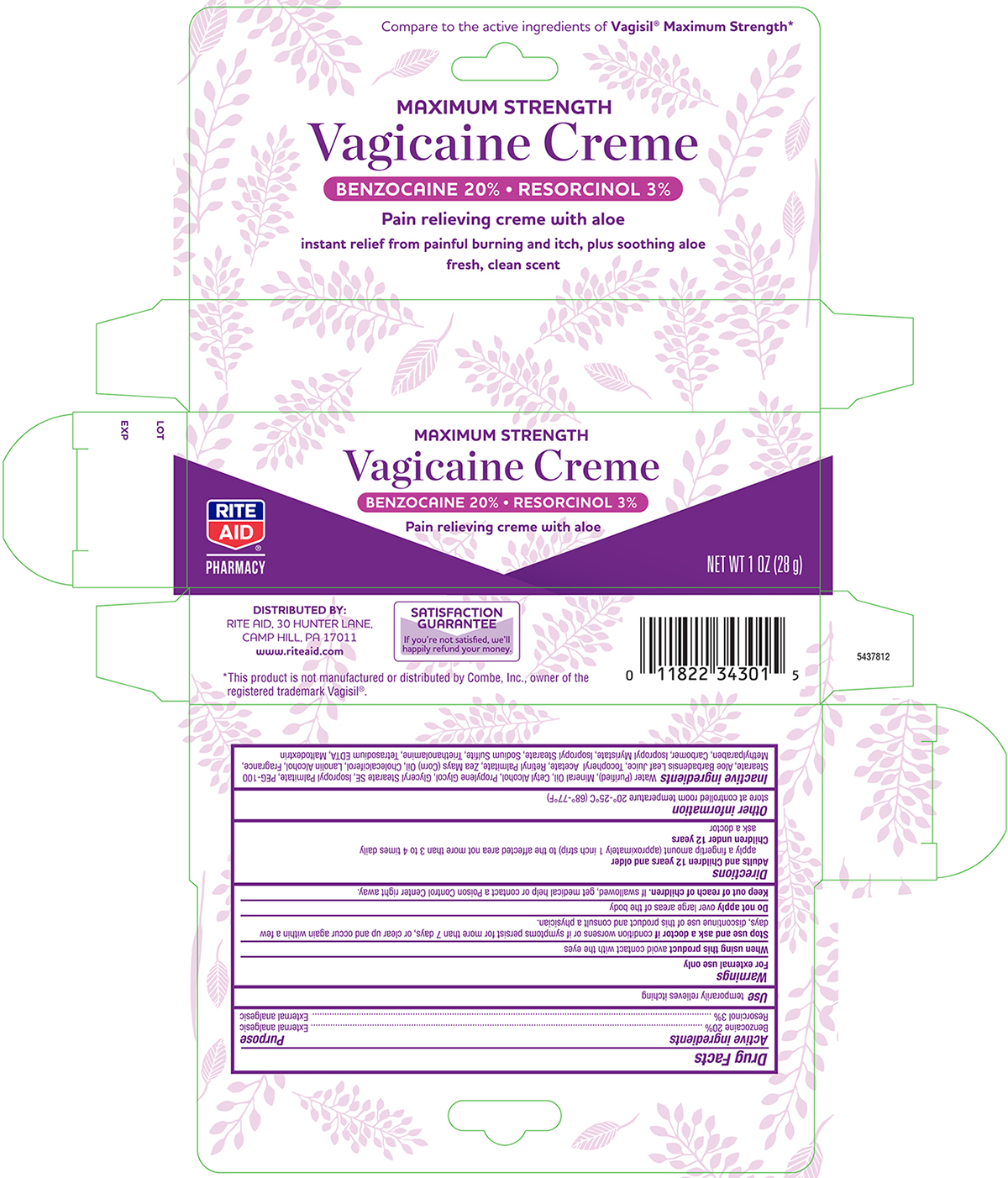 DRUG LABEL: Vagicaine Medicated Maximum Strength
NDC: 11822-5880 | Form: CREAM
Manufacturer: Rite Aid
Category: otc | Type: HUMAN OTC DRUG LABEL
Date: 20241121

ACTIVE INGREDIENTS: BENZOCAINE 200 mg/1 g; RESORCINOL 30 mg/1 g
INACTIVE INGREDIENTS: WATER; MINERAL OIL; CETYL ALCOHOL; PROPYLENE GLYCOL; GLYCERYL STEARATE SE; PEG-100 STEARATE; ISOPROPYL PALMITATE; ALOE VERA LEAF; ALPHA-TOCOPHEROL ACETATE; VITAMIN A PALMITATE; CORN OIL; CHOLECALCIFEROL; LANOLIN ALCOHOLS; METHYLPARABEN; CARBOMER HOMOPOLYMER TYPE B (ALLYL PENTAERYTHRITOL CROSSLINKED); ISOPROPYL MYRISTATE; ISOPROPYL STEARATE; SODIUM SULFITE; TROLAMINE; TRISODIUM HEDTA; MALTODEXTRIN

Rite Aid Vagicaine Maximum Strength Cream

Drug Facts

Active ingredient

Benzocaine 20%

Resorcinol 3%

Purpose

External analgesic

External analgesic

Use

temporarily relieves itching

Warnings

For external use only

Allergy Allert

Do not use this product if you have a history of allergy to local anesthetics such as procaine, butacaine, benzocaine or other –caine anesthetics.

Avoid contact with eyes

in case of contact rinse thoroughly and immediately with water.

Stop use and ask doctor if

condition worsens, or if symptoms persist for more than 7 days, or clear up and occur again within a few days

Keep out of reach of children.

If swallowed, get medical help or contact a Poison Control Center right away.

Directions

Adults and children 12 years and older

Apply a finger tip amount (approxiamtely a 1 inch strip) to the affected areas not more than 3 to 4 times daily

Children under 12 years

ask a doctor

Other Information:

questions?

Inactive ingredients

Water, Mineral Oil, Cetyl Alcohol, Propylene Glycol, Glyceryl Stearate, PEG-100 Stearate, Isopropyl Palmitate, Aloe Barbadensis Leaf Extract, Tocopheryl Acetate, Retinyl Palmitate, Zea Mays (Corn) Oil, Cholecalciferol, Lanolin Alcohol, Fragrance, Methylparaben, Carbomer, Isopropyl Myristate, Isopropyl Stearate, Sodium Sulfite, Triethanolamine, Trisodium EDTA, Maltodextrin

Principal Display Panel- Tube

RITE AID NDC 11822-5880-1

Maximum Strength

Vagicaine Creme

NET WT 1.0 OZ (28 g)

Principal Display Panel- Carton

RITE AID NDC 11822-5880-1

MAXIMUM STRENGTH

VAGICAINE CREAM

NET WT 1.0 OZ (28g)